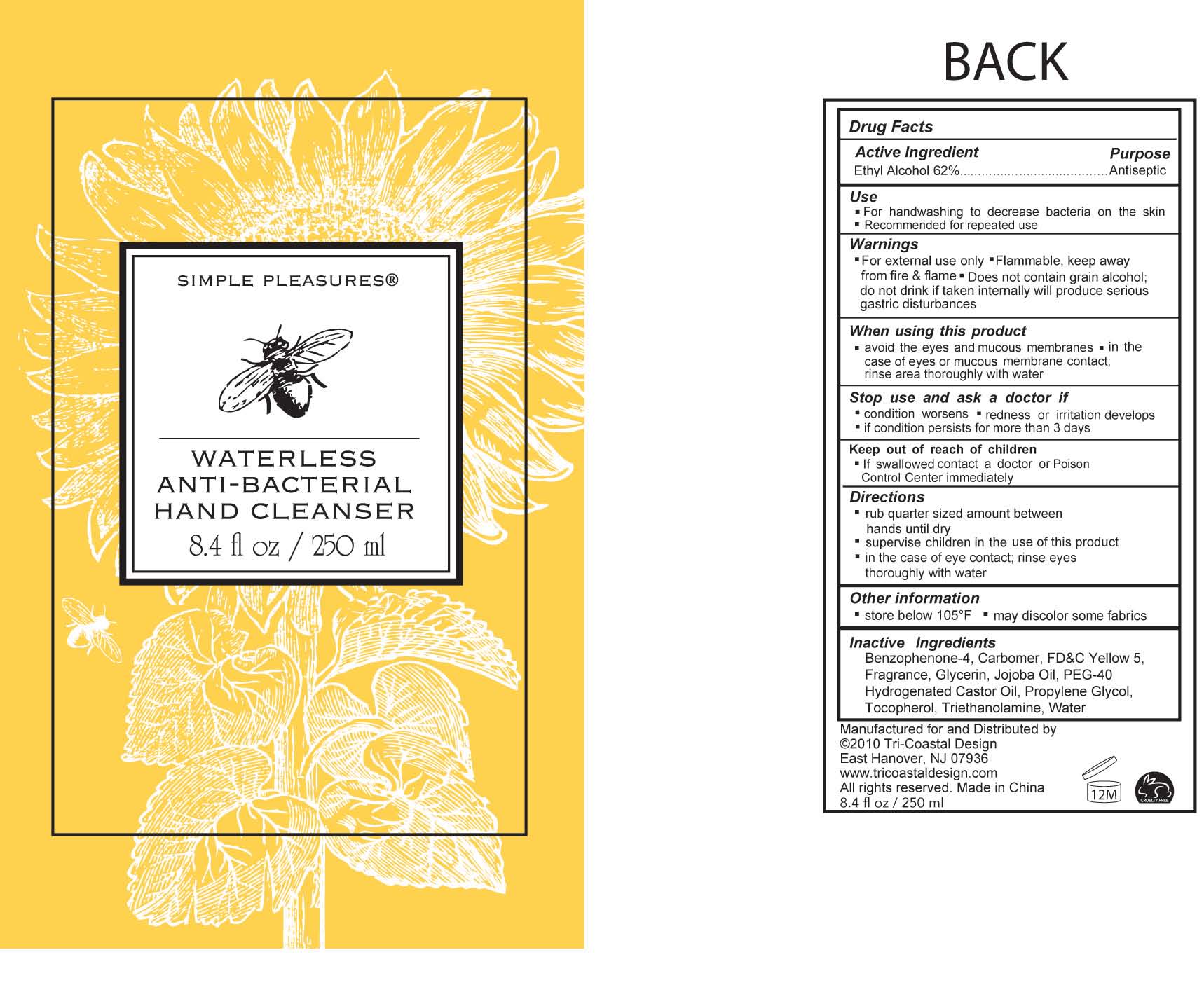 DRUG LABEL: Waterless Anti-Bacterial Hand Cleanser
NDC: 49852-025 | Form: LIQUID
Manufacturer: Tri-Coastal Design Company Inc.
Category: otc | Type: HUMAN OTC DRUG LABEL
Date: 20160607

ACTIVE INGREDIENTS: ALCOHOL 62 mL/100 mL
INACTIVE INGREDIENTS: FD&C YELLOW NO. 5; GLYCERIN; POLYOXYL 40 HYDROGENATED CASTOR OIL; PROPYLENE GLYCOL; ALPHA-TOCOPHEROL; TROLAMINE; WATER

Drug Facts

Active Ingredient

Ethyl Alcohol 62%

Purpose

Antiseptic

Uses

- For handwashing to decrease bacteria on the skin
- Recommended for repeated use

Warnings

- For external use only
- Flammable, keep away from fire and flame
- Does not contain grain alcohol; do not drink, if taken internally will produce serious gastric disturbances

When using this product

- avoid the eyes an mucous membranes
- in the case of eyes or mucous membrane contact; rinse area thoroughly with water

Stop use and ask a doctor if

- condition worsens
- redness or irritation develops
- if condition persists for more than 3 days

Keep out of reach of children

If swallowed contact a doctor or Poison Control Center immediately.

Directions

- rub quarter sized amount between hands until dry
- supervise children in the use of this product
- in the case of eye contact, rinse eyes thoroughly with water

Other information

- store below 105F
- may discolor some fabrics

Inactive Ingredients

Benzophenone-4, Carbomer, FDC Yellow 5, Fragrance, Glycerin, PEG-40 Hydrogenated Castor Oil, Propylene Glycol, Tocopherol, Jojoba Oil, Triethanolamine, Water